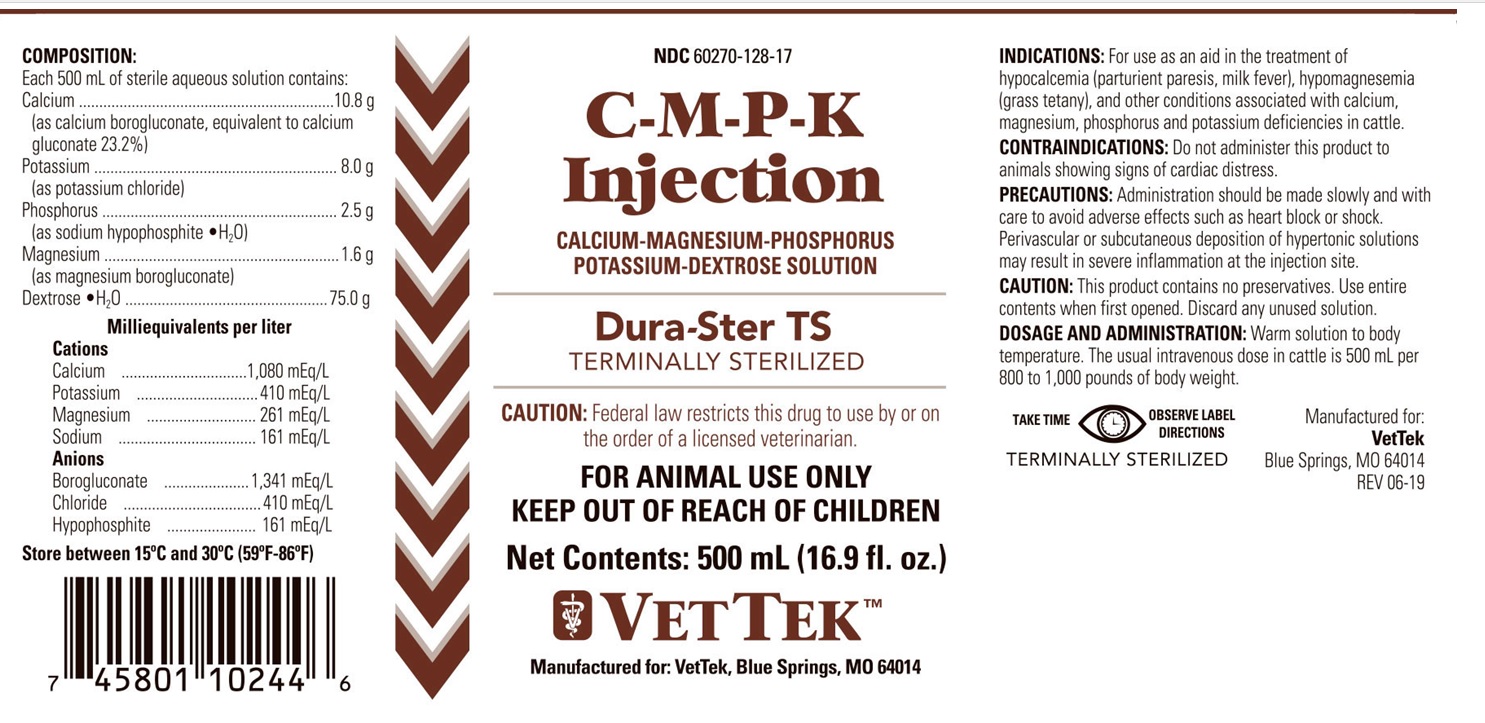 DRUG LABEL: C-M-P-K
NDC: 60270-128 | Form: INJECTION, SOLUTION
Manufacturer: VetTek
Category: animal | Type: PRESCRIPTION ANIMAL DRUG LABEL
Date: 20191101

ACTIVE INGREDIENTS: CALCIUM GLUCONATE MONOHYDRATE 10.8 g/500 mL; POTASSIUM CHLORIDE 8.0 g/500 mL; PHOSPHORUS 2.5 g/500 mL; MAGNESIUM GLUCONATE 1.6 g/500 mL; DEXTROSE MONOHYDRATE 75.0 g/500 mL

C-M-P-K Injection

KEEP OUT OF REACH OF CHILDREN

INDICATIONS:

For use as an aid in the treatment of hypocalcemia (parturient paresis, milk fever), hypomagnesemia (grass tetany), and other conditions associated with calcium, magnesium, phosphorus and potassium deficiencies in cattle.

CONTRAINDICATIONS:

Do not administer this product to animals showing signs of cardiac distress.

PRECAUTIONS:

Administration should be made slowly and with care to avoid adverse effects such as heart block or shock. Perivascular or subcutaneous deposition of hypertonic solutions may result in severe inflammation at the injection site.

CAUTION:

This product contains no preservatives. Use entire contents when first opened. Discard any unused solution.

DOSAGE AND ADMINISTRATION:

Warm solution to body temperature. The usual intravenous dose in cattle is 500 mL per 800 to 1,000 pounds of body weight.

STORAGE AND HANDLING

Store between 15°C and 30°C (59°F and 86°F)

VETERINARY INDICATIONS

FOR ANIMAL USE ONLY

CAUTION:

Federal law restricts this drug to use by or on the order of a licensed veterinarian.

COMPOSITION:

Each 500 mL of sterile aqueous solution contains:
Calcium............................10.8 g
(as calcium borogluconate, equivalent to calcium gluconate 23.2%)
Potassium..........................8.0 g
(as potassium chloride)
Phosphorus.......................2.5 g
(as sodium hypophosphite • H2O)
Magnesium.......................1.6 g
(as magnesium borogluconate)
Dextrose •H2O................75.0 g
Milliequivalents per liter

Cations
Calcium......................1,080 mEq/L
Potassium.....................410 mEq/L
Magnesium...................261 mEq/L
Sodium.........................161 mEq/L

Anions
Borogluconate....................1,341 mEq/L
Chloride................................410 mEq/L
Hypophosphite......................161 mEq/L

INFORMATION FOR OWNERS/CAREGIVERS

Manufactured for
VetTek
Blue Springs, MO 64014

REV 06-19

PACKAGE LABEL

NDC 60270-128-17

C-M-P-K Injection

CALCIUM-MAGNESIUM-PHOSPHORUS-POTASSIUM-DEXTROSE SOLUTION

Dura-Ster TS

TERMINALLY STERILIZED

Net Contents: 500 mL (16.9 fl. oz.)